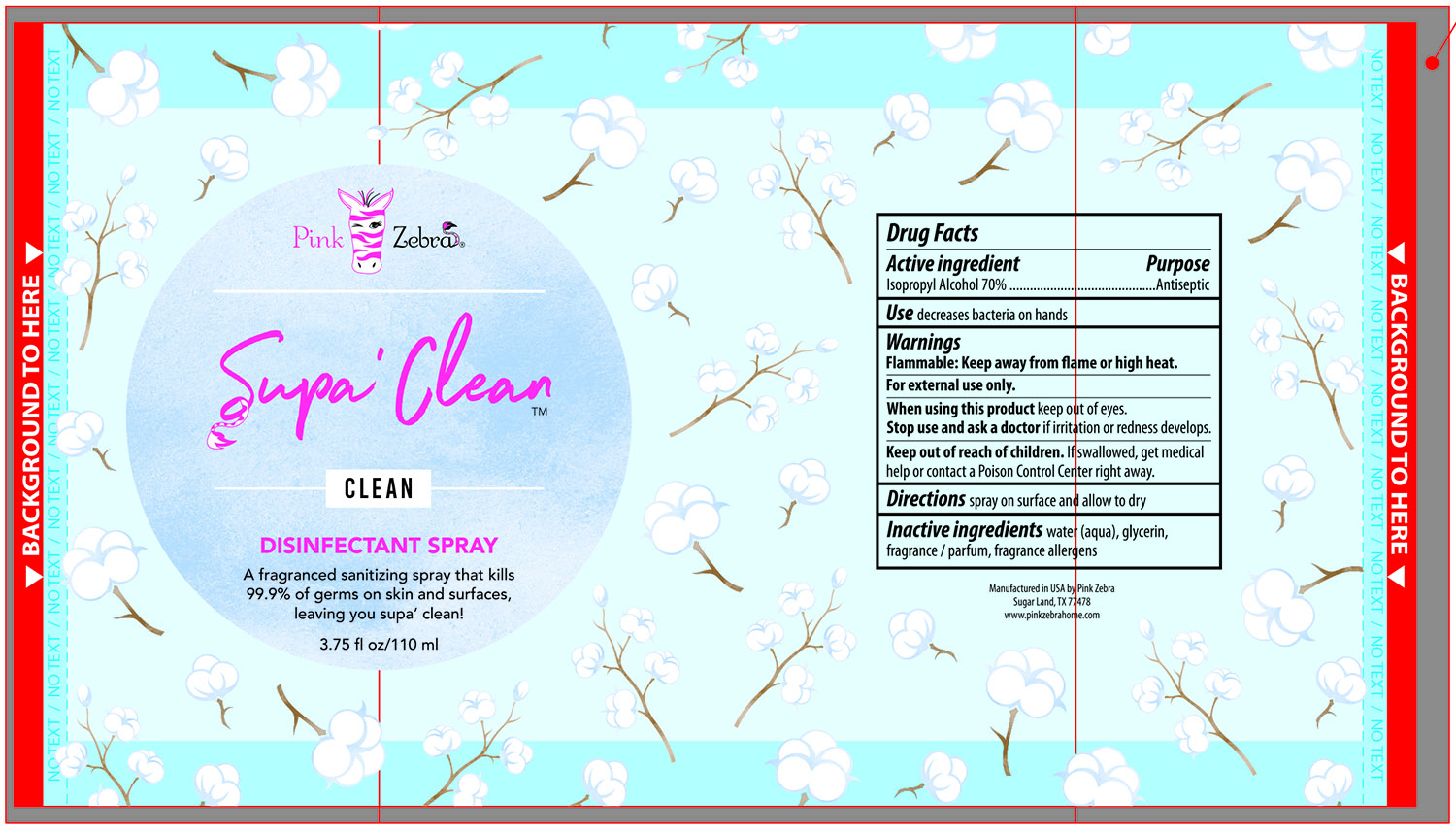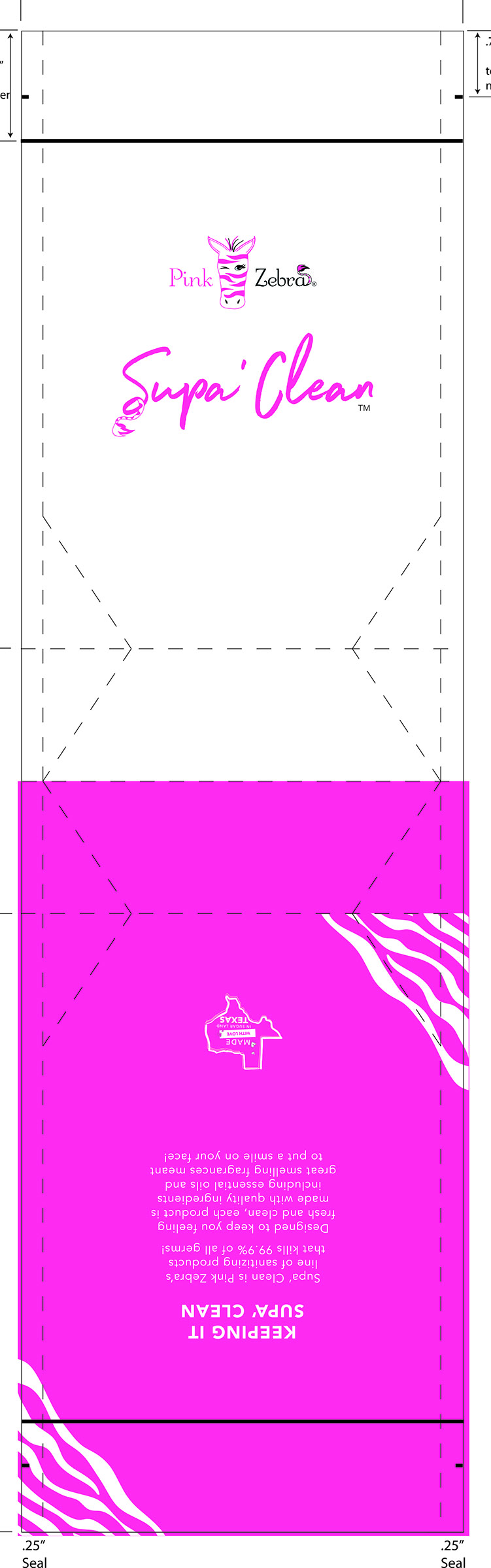 DRUG LABEL: Supa Clean Disinfectant
NDC: 75635-021 | Form: SPRAY
Manufacturer: Light House Candles, LLC
Category: otc | Type: HUMAN OTC DRUG LABEL
Date: 20200522

ACTIVE INGREDIENTS: ISOPROPYL ALCOHOL 70 mL/100 mL
INACTIVE INGREDIENTS: WATER; GLYCERIN

SUPA CLEAN Disinfectant - DisinfectantLight House Candles, LLC